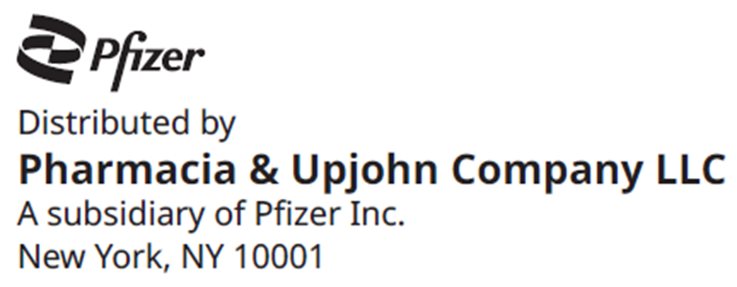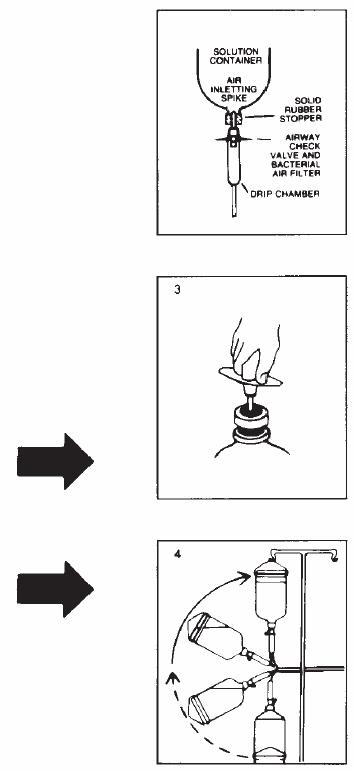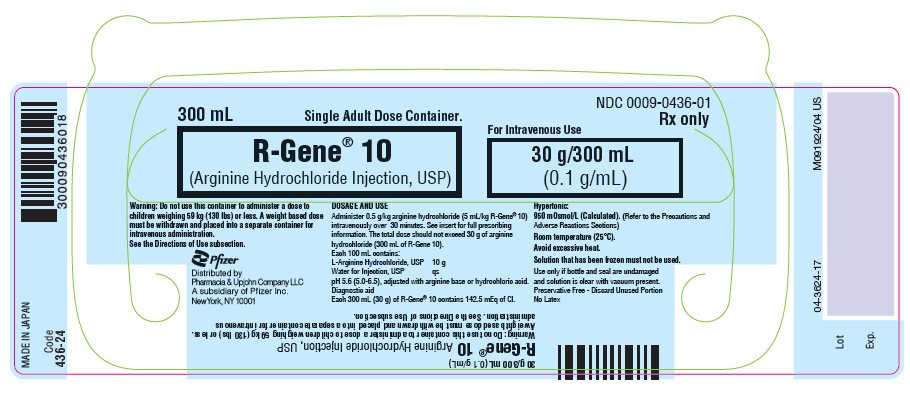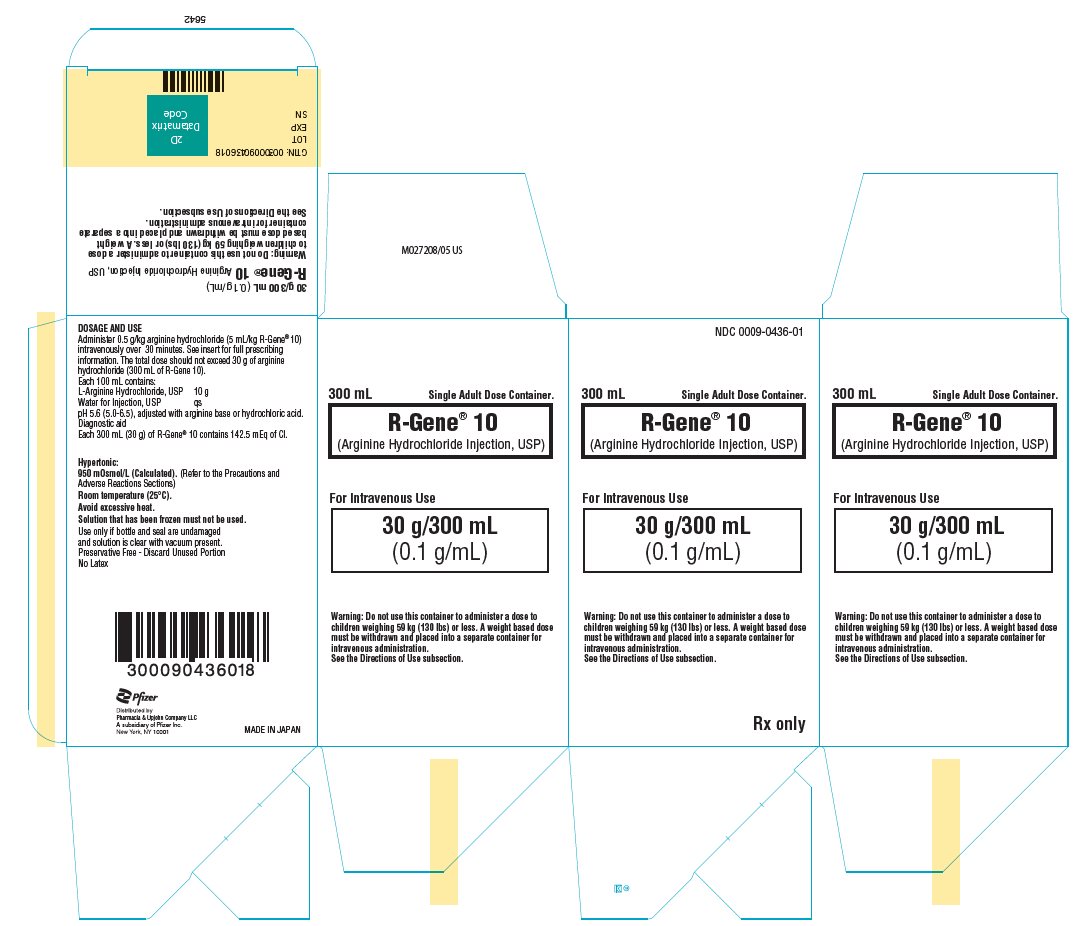 DRUG LABEL: R-Gene
NDC: 0009-0436 | Form: INJECTION, SOLUTION
Manufacturer: Pharmacia & Upjohn Company LLC
Category: prescription | Type: HUMAN PRESCRIPTION DRUG LABEL
Date: 20240402

ACTIVE INGREDIENTS: ARGININE HYDROCHLORIDE 10 g/100 mL
INACTIVE INGREDIENTS: WATER; HYDROCHLORIC ACID

R-Gene® 10
Arginine Hydrochloride Injection, USP

For Intravenous Use

DESCRIPTION

Each 100 mL of R-Gene® 10 (Arginine Hydrochloride Injection, USP) for intravenous use contains 10 g of L-Arginine Hydrochloride, USP in Water for Injection, USP (equivalent to a 10% solution) (0.1 g/mL). L-arginine is a naturally occurring amino acid.

R-Gene® 10 is hypertonic (950 mOsmol/liter) and contains 47.5 mEq of chloride ion per 100 mL of solution. The pH is adjusted to 5.6 (5.0–6.5) with arginine base or hydrochloric acid.

CLINICAL PHARMACOLOGY

Intravenous infusion of R-Gene® 10 often induces a pronounced rise in the plasma level of human growth hormone (HGH) in subjects with intact pituitary function. This rise is usually diminished or absent in patients with impairment of this function.

Expected Plasma Levels of HGH in ng/mL
Patient | Control Range | Range of Peak Response to Arginine
Normal | 0–6 | 10–30
Pituitary
deficient | 0–4 | 0–10

These ranges are based on the mean values of plasma HGH levels calculated from the data of several clinical investigators and reflect their experiences with various methods of radioimmunoassay. Upon gaining experience with this diagnostic test, each clinician will establish his/her own ranges for control and peak levels of HGH.

L-arginine is a normal metabolite in animals and man and has a low order of toxicity.

INDICATIONS AND USAGE

R-Gene® 10 is indicated as an intravenous stimulant to the pituitary for the release of human growth hormone in patients where the measurement of pituitary reserve for HGH can be of diagnostic usefulness. It can be used as a diagnostic aid in such conditions as panhypopituitarism, pituitary dwarfism, chromophobe adenoma, postsurgical craniopharyngioma, hypophysectomy, pituitary trauma, acromegaly, gigantism and problems of growth and stature.

If the insulin hypoglycemia test has indicated a deficiency of pituitary reserve for HGH, a test with R-Gene® 10 is advisable to confirm the negative response. This can be done after a waiting period of one day. As patients may not respond to R-Gene® 10 (Arginine Hydrochloride Injection, USP) during the first test, the unresponsive patient should be tested again to confirm the negative result. A second test can be performed after a waiting period of one day. Some patients who respond to R-Gene® 10 do not respond to insulin and vice versa. The rate of false positive responses for R-Gene® 10 is approximately 32%, and the rate of false negatives is approximately 27%.

CONTRAINDICATIONS

The administration of R-Gene® 10 is contraindicated in persons having known hypersensitivity to any ingredient in this product.

WARNINGS

There have been reports of overdosage of R-Gene® 10 in pediatric patients leading to death. EXTREME CAUTION MUST BE EXERCISED WHEN INFUSING R-GENE® 10 INTO PEDIATRIC PATIENTS. OVERDOSAGE OF R-GENE® 10 IN PEDIATRIC PATIENTS CAN RESULT IN HYPERCHLOREMIC METABOLIC ACIDOSIS, CEREBRAL EDEMA, OR POSSIBLY DEATH.

Hypersensitivity reactions, including anaphylaxis have been reported. Appropriate medical support should be available during R-Gene® 10 administration. If anaphylaxis or other serious hypersensitivity reaction occurs, R-Gene® 10 should be discontinued and appropriate medical treatment initiated.

R-Gene® 10 should always be administered by intravenous infusion because of its hypertonicity.

R-Gene® 10 is a diagnostic aid and is not intended for therapeutic use.

PRECAUTIONS

General

R-Gene® 10 is a hypertonic (950 mOsmol/liter) and acidic (average pH of 5.6) solution that can cause irritation and damage to tissues. Care should be used to ensure administration of R-Gene® 10 through a patent catheter within a patent vein. Excessive rates of infusion may result in local irritation and in flushing, nausea, or vomiting. Inadequate dosing or prolongation of the infusion period may diminish the stimulus to the pituitary and nullify the test.

The arginine in R-Gene® 10 can be metabolized resulting in nitrogen-containing products for excretion. The effect of an acute amino acid or nitrogen burden upon patients with impairment of renal function should be considered when R-Gene® 10 is to be administered.

The chloride content of R-Gene® 10 is 47.5 mEq per 100 mL of solution, and the effect of infusing this amount of chloride into patients with electrolyte imbalance should be evaluated before the test is undertaken.

It should be noted that the basal and post stimulation levels of growth hormone are elevated in patients who are pregnant or are taking oral contraceptives.

Carcinogenesis, mutagenesis, and impairment of fertility

Long term animal studies have not been performed to evaluate the carcinogenic potential, the mutagenic potential or the effect on fertility of intravenously administered R-Gene® 10.

Pregnancy

Reproduction studies have been performed in rabbits and mice at doses 12 times the human dose and have revealed no evidence of impaired fertility or harm to the fetus due to R-Gene® 10 (10% Arginine Hydrochloride Injection, USP). There have been no adequate or well controlled studies for the use of R-Gene® 10 in pregnant women. Because animal reproduction studies are not always predictive of human response, this drug should not be used during pregnancy.

Nursing Mothers

It is not known whether intravenous administration of R-Gene® 10 could result in significant quantities of arginine in breast milk. Systemically administered amino acids are secreted into breast milk in quantities not likely to have a deleterious effect on the infant. Nevertheless, caution should be exercised when R-Gene® 10 is to be administered to nursing women.

Geriatric Use

Clinical studies of arginine did not include a sufficient number of subjects aged 65 and over to determine whether they respond differently from younger subjects. Other reported clinical experience has not identified differences in responses between the elderly and younger patients.

ADVERSE REACTIONS

Adverse reactions associated with 1670 infusions in premarketing studies were as follows:

Non-specific side effects consisting of nausea, vomiting, headache, flushing, numbness and local venous irritation were reported in approximately 3% of the patients.

One patient had an allergic reaction which was manifested as a confluent macular rash with reddening and swelling of the hands and face. The rash subsided rapidly after the infusion was terminated and 50 mg of diphenhydramine were administered. One patient had an apparent decrease in platelet count from 150,000 to 60,000. One patient with a history of acrocyanosis had an exacerbation of this condition following infusion of R-Gene® 10.

Post Marketing Experience:

The following adverse events have been reported during post-marketing use: extravasation leading to burn-like reaction and/or skin necrosis requiring surgical intervention, hypersensitivity reactions including anaphylaxis, and hematuria that in some cases occurred 1–2 days after an R-Gene® 10 administration. Because these adverse events are reported voluntarily from a population of uncertain size, it is not always possible to reliably estimate their frequency or establish a causal relationship to drug exposure.

OVERDOSAGE

An overdosage may cause a transient metabolic acidosis with hyperventilation, which could lead to death (see "WARNINGS"). In most cases the acidosis will self-compensate and the base deficit will return to normal following completion of the infusion. If the condition persists, the deficit should be determined and corrected by a calculated dose of an alkalizing agent.

DOSAGE AND ADMINISTRATION

Adult Dosage

The recommended adult dose is 30 g arginine hydrochloride (300 mL of R-Gene® 10) administered by intravenous infusion over 30 minutes. The total dose should not exceed 30 g arginine hydrochloride. See Directions for Use for preparation instructions.

Pediatric Dosage

The recommended pediatric dose is 0.5 g/kg arginine hydrochloride (5 mL/kg of R-Gene® 10) administered by intravenous infusion over 30 minutes. The total dose should not exceed 30 g arginine hydrochloride.

- For patients weighing 59 kg or less, withdraw a weight based dose from a sealed R-Gene® 10 bottle and place in a separate container for intravenous infusion to avoid the inadvertent delivery and administration of the total volume from the commercially available container. See Directions for Use for preparation instructions.
- For patients weighing 60 kg or more, the recommended dose is 30 g arginine hydrochloride (300 mL of R-Gene® 10). See Directions for Use for preparation instructions

Test Procedure

The intravenous infusion of R-Gene® 10 is a part of the test for measurement of pituitary reserve of human growth hormone and, for successful administration of the test, clinical conditions and procedures should be as follows:

1. The test should be scheduled in the morning following a normal night's sleep, and an overnight fast should continue through the test period.
2. Patients must be placed at bed rest for at least 30 minutes before the infusion begins. Care should be taken to minimize apprehension and distress. This is particularly important in children.
3. R-Gene® 10 (Arginine Hydrochloride Injection, USP) is a hypertonic solution and should only be infused through an indwelling needle or soft catheter placed in an antecubital vein or other suitable vein (see PRECAUTIONS). Blood samples should be taken by venipuncture from the contra-lateral arm.
4. A desirable schedule for drawing blood samples is at −30, 0, 30, 60, 90, 120 and 150 minutes.
5. R-Gene® 10 should be infused beginning at zero time at a uniform rate which will permit the recommended dose to be administered over 30 minutes.
6. Blood samples should be promptly centrifuged and the plasma stored at −20°C until assayed by one of the published radioimmunoassay procedures.
7. Diagnostic test results showing a deficiency of pituitary reserve for HGH should be confirmed by a second test with R-Gene® 10, or one may elect to confirm with the insulin hypoglycemia test. A waiting period of one day is advised between tests.

Directions for Use

R-Gene® 10 is provided as a ready-to-use solution for patients weighing 60 kg (132 lbs) or more and should not be further diluted. For pediatric patients weighing 59 kg (130 lbs) or less a dose must be placed in a separate container. Follow the preparation instructions below.

Parenteral drug products should be inspected visually for particulate matter and discoloration prior to administration whenever solution and container permit.

For Pediatric Patients weighing 59 kg (130 lbs) or less:

Withdraw a weight-based dose from an intact sealed bottle of R-Gene® 10. The entire 300 mL bottle of R-Gene® 10 for infusion is not intended for use in patients weighing 59 kg or less. The dose must be placed in a separate container, such as an evacuated sterile glass container designed for intravenous administration, using aseptic technique.

Additionally, R-Gene® 10 is stable in polypropylene syringes and plastic containers made of either polyvinyl chloride (PVC) or ethylene vinyl acetate (EVA).

The post-penetration storage period is not more than 4 hours including infusion time at room temperature or 24 hours at refrigerated temperature (2-8°C).

The healthcare professional administering the dose should verify the accuracy of the dose prior to administration.

Use only if the solution is clear. Discard any unused drug product.

For Adults and Pediatric Patients weighing 60kg (132 lbs) or more:

Follow these directions using aseptic technique. As R-Gene® 10 for intravenous use is provided in glass containers, a standard air-inletting, air-filtering intravenous infusion set with a bacterial air filter is required.

1. Use only if solution is clear and seal is intact. Carefully examine bottle for evidence of damage, e.g., small cracks, dents in seal, or areas of dried powder on exterior. Do not administer contents if such damage is found.
2. Remove plastic flip off lid from bottle to expose rubber stopper, taking care that you do not contaminate the target site of the stopper with fingers, hair, clothing, etc. Immediately perform step #3.
3. With shut-off clamp closed, remove sterility protector from spike of administration set and immediately insert set with a quick thrust into center of stopper with bottle upright on table. (Push straight in — don't twist — twisting may cause stopper coring.)
4. Promptly invert bottle to automatically establish fluid level in drip chamber and to check for vacuum by observing rising filtered air bubbles. Discard bottle if there is no vacuum or if the solution is not clear.
5. Clear tubing of air. Proceed with infusion.

HOW SUPPLIED

R-Gene® 10 is supplied as a 30 g/300 mL (0.1 g/mL) fill in 500 mL glass containers.

Preservative Free: Discard any unused portion.

NDC 0009-0436-01

Exposure of pharmaceutical products to heat should be minimized. Avoid excessive heat. It is recommended that the product be stored at room temperature (25°C); however, brief exposure up to 40°C does not adversely affect the product. Solution that has been frozen must not be used.

LAB-0020-13.0
Revised Aug 2023

PRINCIPAL DISPLAY PANEL - 300 mL Container Label

NDC 0009-0436-01
Rx only

300 mL
Single Adult Dose Container.

R-Gene®10
(Arginine Hydrochloride Injection, USP)

For Intravenous Use

30 g/300 mL
(0.1 g/mL)

Pfizer
Distributed by
Pharmacia & Upjohn Company LLC
A subsidiary of Pfizer Inc.
New York, NY 10001

PRINCIPAL DISPLAY PANEL - 300 mL Container Carton

NDC 0009-0436-01

300 mL
Single Adult Dose Container.

R-Gene® 10
(Arginine Hydrochloride Injection, USP)

For Intravenous Use

30 g/300 mL
(0.1 g/mL)

Warning: Do not use this container to administer a dose to
children weighing 59 kg (130 lbs) or less. A weight based dose
must be withdrawn and placed into a separate container for
intravenous administration.
See the Directions of Use subsection.

Rx only